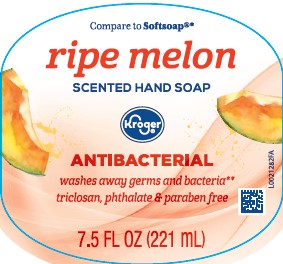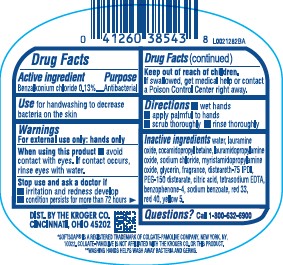 DRUG LABEL: Moisturizing Antibacterial
NDC: 30142-826 | Form: SOAP
Manufacturer: The Kroger Co.
Category: otc | Type: HUMAN OTC DRUG LABEL
Date: 20260227

ACTIVE INGREDIENTS: BENZALKONIUM CHLORIDE 1.3 mg/1 mL
INACTIVE INGREDIENTS: WATER; LAURAMINE OXIDE; COCAMIDOPROPYL BETAINE; LAURAMIDOPROPYLAMINE OXIDE; SODIUM CHLORIDE; MYRISTAMIDOPROPYLAMINE OXIDE; GLYCERIN; DISTEARETH-75 ISOPHORONE DIISOCYANATE; PEG-150 DISTEARATE; CITRIC ACID MONOHYDRATE; SULISOBENZONE; SODIUM BENZOATE; D&C RED NO. 33; FD&C RED NO. 40; FD&C YELLOW NO. 5

Kroger 279.003/279AD-AE
Light Moisturizing Antibacterial Hand Soap

Active ingredient

Benzalkonium Chloride 0.13%

Purpose

Antibacterial

Use

for handwashing to decrease bacteria on the skin

Warnings

For external use only: hands only

When using this product

avoid contact with eyes. If contact occurs, rinse eyes thoroughly with water.

Stop use and ask a doctor if

- irritation and redness develop
- condition persists for more than 72 hours

Keep out of reach of children.

If swallowed, get medical help or contact a Poison Control Center right away.

Directions

- wet hands
- apply palmful to hands
- scrub thoroughly
- rinse thoroughly

Inactive ingredients

water, lauramine oxide, cocamidopropyl betaine, lauramidopropylamine oxide, sodium chloride, myristamidopropylamine oxide, glycerin, fragrance, disteareth-75 IPDI, PEG-150 distearate, citric acid, tetrasodium EDTA, benzophenone-4, sodium benzoate, red 33, red 40, yellow 5

Questions?

Call 1-800-632-6900

Adverse reactions

DIST. BY THE KROGER CO.

CINCINNATI, OHIO 45202

Disclaimer/Claim

SOFTSOAP IS A REGISTERED TRADEMARK OF COLGATE-PAMOLIVE COMPANY, NEW YORK, NY, 10022. COLGATE-PAMOLIVE IS NOT AFFILIATED WITH THE KROGER CO. OR THIS PRODUCT.

**WASHING HANDS HELPS WASH AWAY BACTERIA AND GERMS.

Principal display panel

Compare to Softsoap®*

ripe melon

SCENTED HAND SOAP

Kroger®

ANTIBACTERIAL

washes away germs and bacteria**

triclosan, phthalate & paraben free

7.5 FL OZ (221 mL)